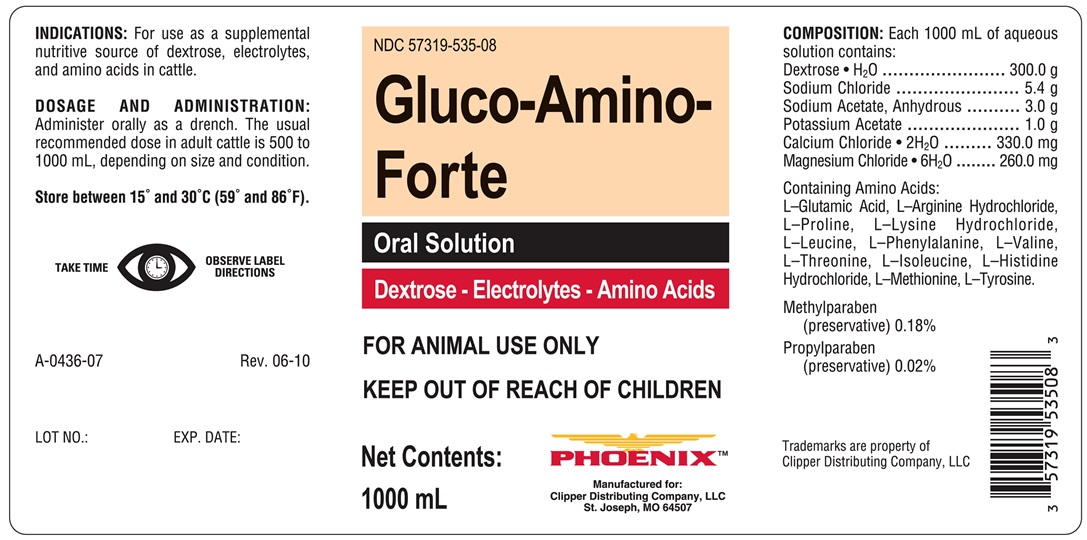 DRUG LABEL: Gluc-Amino-Forte
NDC: 57319-535 | Form: SOLUTION
Manufacturer: Clipper Distributing Company, LLC
Category: animal | Type: OTC ANIMAL DRUG LABEL
Date: 20180425

ACTIVE INGREDIENTS: CALCIUM CHLORIDE 330 mg/1000 mL; DEXTROSE MONOHYDRATE 300 g/1000 mL; MAGNESIUM CHLORIDE 260 mg/1000 mL; POTASSIUM ACETATE 1 g/1000 mL; SODIUM ACETATE ANHYDROUS 3 g/1000 mL; SODIUM CHLORIDE 5.4 g/1000 mL

GLUCAMINOLYTE FORTE

INDICATIONS AND USAGE

Oral Solution

Dextrose - Electrolytes - Amino Acids

FOR ANIMAL USE ONLY

KEEP OUT OF REACH OF CHILDREN

INDICATIONS

For use as a supplemental nutritive source of electrolytes, dextrose and amino acids in cattle.

DOSAGE AND ADMINISTRATION

Administer orally as a drench. The usual recommended dose in adult cattle is 500 to 1000 mL, depending on size and condition.

STORAGE AND HANDLING

STORE AT CONTROLLED ROOM TEMPERATURE BETWEEN 15° and 30°C (59° and 86°)

TAKE TIME OBSERVE LABEL DIRECTIONS

COMPOSITION

Each 1000 mL of aqueous solution contains:

Dextrose • H2O ........................... 300 g
Sodium Chloride ........................... 5.4 g
Sodium Acetate, Anhydrous .......... 3.0 g
Potassium Acetate ....................... 1.0 g
Calcium Chloride • 2H2O ........ 330.0 mg
Magnesium Chloride • 5H2O ... 260.0 mg

Containing Amino Acids:

L-Glutamic Acid, L-Arginine, Hydrochloride, L-Proline, L-Lysine Hydrochloride, L-Leucine, L-Phenylalanine, L-Valine, L-Threonine, L-Isoleucine, L-Histidine Hydrochloride, L-Methionine, L-Tyrosine.

Methylparaben (preservative) 0.18% and Propylparaben (preservative) 0.02%.